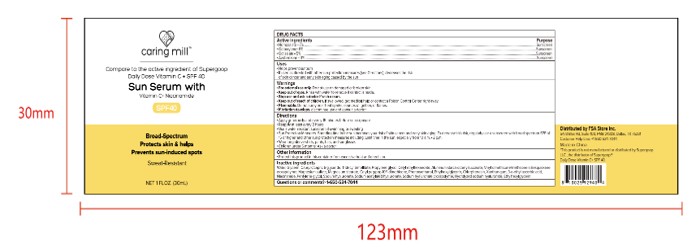 DRUG LABEL: Caring mill sun serum with Vitamin C Niacinamide
NDC: 81522-229 | Form: LIQUID
Manufacturer: FSA Store lnc.
Category: otc | Type: HUMAN OTC DRUG LABEL
Date: 20260125

ACTIVE INGREDIENTS: OCTOCRYLENE 6 g/100 mL; OCTISALATE 5 g/100 mL; AVOBENZONE 3 g/100 mL; HOMOSALATE 7 g/100 mL
INACTIVE INGREDIENTS: SODIUM HYALURONATE; PROPYLENE GLYCOL; VINYL DIMETHICONE/METHICONE SILSESQUIOXANE CROSSPOLYMER; MAGNESIUM STEARATE; PHENOXYETHANOL; CHLORPHENESIN; SODIUM ACETYLATED HYALURONATE; MAGNESIUM SULFATE; CAPRYLIC/CAPRIC TRIGLYCERIDE; SODIUM HYALURONATE CROSSPOLYMER-6; NIACINAMIDE; ALUMINUM STARCH OCTENYLSUCCINATE; CETYL PEG/PPG-10/1 DIMETHICONE (HLB 3.7); TRIDECYL TRIMELLITATE; ETHYLHEXYLGLYCERIN; PENTYLENE GLYCOL; CETYL ETHYLHEXANOATE; XANTHAN GUM; AQUA

ACTIVE INGREDIENT

HOMOSALATE
OCTOCRYLENE
OCTISALATE
AVOBENZONE

PURPOSE

.Helps prevent sunbum
.If used as directed with other sun protection measures (see Directions), decreases the riskof skin cancer and early skin aging caused by the sun

WARNINGS

Warnings+For external use only.Do not use on damaged or broken skin..Keep out of eyes. Rinse with water to remove if contactis made.
.Stop use and ask a doctor if rash occurs.
.Keep out of reach of children,If swallowed,get medical help or contact a Poison Control Center right away.*Flammable.Do not spray near heat sparks,sources ofignition, or flames,.If irritation develops.discontinue use and consult a doctor.

Keep out of reach of children, If swallowed,get medical help or contact a Poison Controf Center right away

DOSAGE AND ADMINISTRATION

*Apply generously and evenly 15 minutes before sun exposure+Reapplv at least everv 2 hours

INDICATIONS AND USAGE

+Use a water resistant sunscreen if swimming or sweating.Sun Protection Messures,Spending ime in the sun increases yourisk of skin cane nd eary skin aging. To decrease this isk,regudarlyuse a sunscreen with broad spectrum SPF of15 or higher and other sun protection measures including: Limit time in the sun,especially from 10 a.m,-2 p.m.
* Wear long-sleeve shints,pants,hats,and sunglasses*Children under 6 months: Ask a doctor

INACTIVE INGREDIENT

WATER
GLYCERIN
CAPRYLIC/CAPRIC TRIGLYCERIDE
TRIDECYL TRIMELLITATE
PROPYLENE GLYCOL
CETYL ETHYLHEXANOATE
ALUMINUM STARCH OCTENYLSUCCINATE
VINYL DIMETHICONE/METHICONE SILSESQUIOXANE CROSSPOLYMER
MAGNESIUM SULFATE
MAGNESIUM STEARATE
CETYL PEG/PPG-10/1 DIMETHICONE
PHENOXYETHANOL
ETHYLHEXYLGLYCERIN
CHLORPHENESIN
XANTHAN GUM
3-o-ETHYL ASCORBIC ACID
NIACINAMIDE
PENTYLENE GLYCOL
SODIUM HYALURONATE
SODIUM ACETYLATED HYALURONATE
SODIUM HYALURONATE CROSSPOLYMER
HYDROLYZED SODIUM HYALURONATE
ETHYLHEXYLGLYCERIN